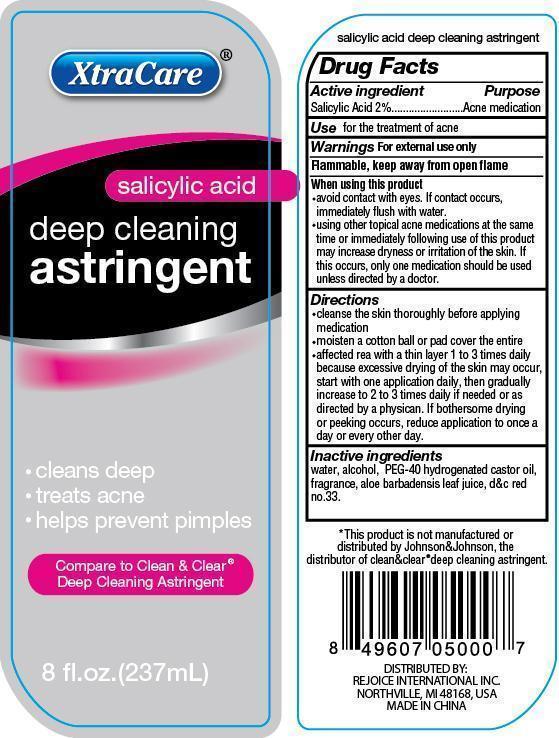 DRUG LABEL: XtraCare Foaming Facial Cleanser
NDC: 57337-036 | Form: GEL
Manufacturer: Rejoice International
Category: otc | Type: HUMAN OTC DRUG LABEL
Date: 20240228

ACTIVE INGREDIENTS: TRICLOSAN 1 mg/237 mg
INACTIVE INGREDIENTS: WATER; SODIUM C14-16 OLEFIN SULFONATE; COCAMIDOPROPYL BETAINE; POLYOXYL 40 CASTOR OIL; DMDM HYDANTOIN; EDETATE DISODIUM; CITRIC ACID MONOHYDRATE; METHYLPARABEN; PROPYLPARABEN; FD&C YELLOW NO. 5; D&C RED NO. 33

XtraCare Foaming Facial Cleanser

Active Ingredient Purpose

Triclosan 0.25% ........................... Antiseptic

PURPOSE

XtraCare (oil-free) foaming facial cleanser

medicated to kill problem-causing bacteria without overdrying

Compare to Clean & Clear® Foaming Facial Cleanser

8 fl. oz. (237 mL)

oil free foaming facial cleanser

Keep out of reach of children. if swallowed, get medical help or contact a Poison Control Center right away.

INDICATIONS AND USAGE

Use to help reduce bacteria on the skin

Warnings For external use only

When using this product avoid contact with eyes. if eye contact occurs, immediately flush with water.

Stop use and ask a doctor if

- excessive skin irritation develops or condition worsens
- symptoms last more than 7 days or clear up and occur again within a few days

Directions

mix in hands with water. Work into a foamy later. Smooth over face and neck. Rinse thoroughly.

Other Information

Do not store where water may enter bottle.

*This product is not manufactured or distributed by Johnson&Johnson, the distributor of clean&clear®foaming facial cleanser.

DISTRIBUTED BY:

REJOICE INTERNATIONAL INC.

NORTHVILLE, MI 48168 USA

MADE IN CHINA

Inactive Ingredients

water, sodium c14-16 olefin sulfonate, cocamide betaine, glycerin, PEG-40 hydrogenated castor oil, fragrance, DMDM hydantoin, disodium EDTA, citric acid, methylparaben, propylparaben, fd&c yellow no.5, d&c red no.33